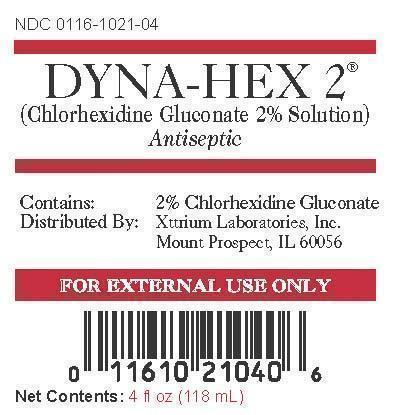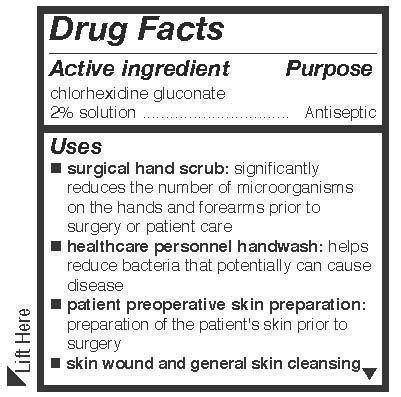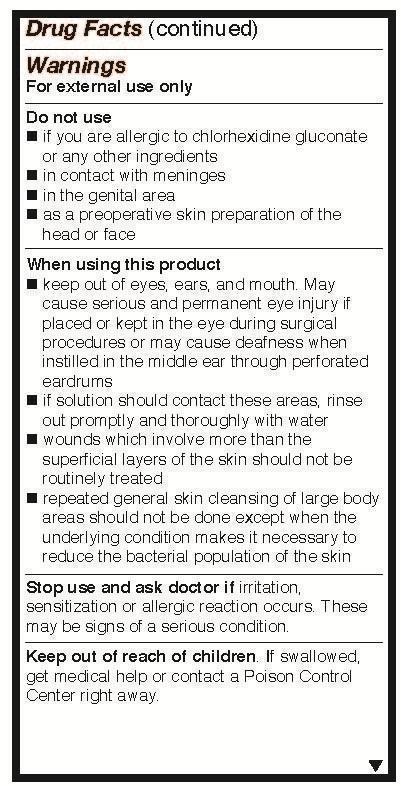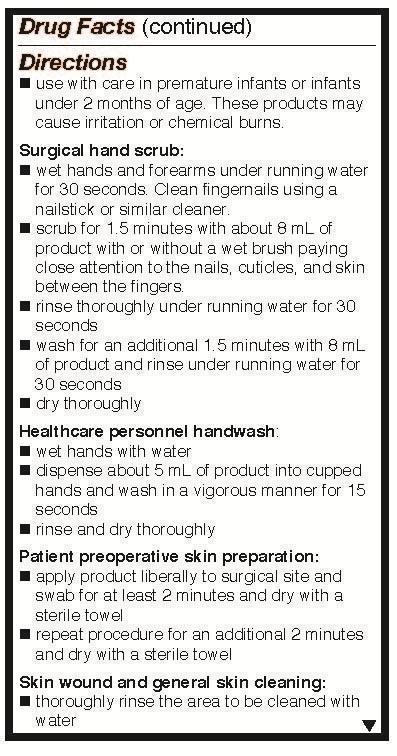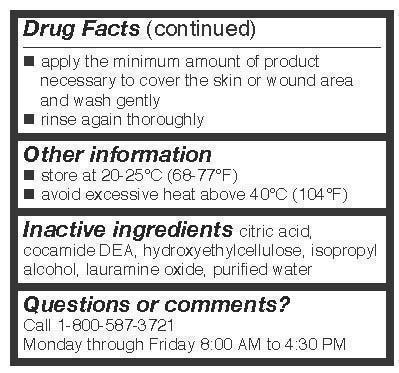 DRUG LABEL: Dyna-Hex
NDC: 67659-901 | Form: LIQUID
Manufacturer: Team Technologies, Inc
Category: otc | Type: HUMAN OTC DRUG LABEL
Date: 20191024

ACTIVE INGREDIENTS: CHLORHEXIDINE GLUCONATE 2 g/100 mL
INACTIVE INGREDIENTS: CITRIC ACID MONOHYDRATE; COCO DIETHANOLAMIDE; HYDROXYETHYL CELLULOSE (2000 CPS AT 1%); ISOPROPYL ALCOHOL; LAURAMINE OXIDE; WATER

Drug Facts

ACTIVE INGREDIENT

Chlorhexidine gluconate 2% Solution

Purposes

surgical hand scrub
healthcare personnel handwash
patient operative skin preparation
skin wound and general skin cleansing

Uses

- surgical hand scrub: significantly reduces the number of microorganisms on the hands and forearms prior to surgery or patient care
- healthcare personnel handwash: helps reduce bacteria that potentially can cause disease
- patient preoperative skin preparation: preparation of the patient's skin prior to surgery
- skin wound and general cleansing

Warnings

For external use only

Do not use

- if you are allergic to chlorhexidine gluconate or any other ingredients
- in contact with meninges
- in the genital area
- as a preoperative skin preparation of the head or face

When using this product

- keep out of eyes, ears, and mouth. May cause serious and permanent eye injury if placed or kept in the eye during surgical procedures or may cause deafness when instilled in the middle ear through perforated eardrums
- if solution should contact these areas, rinse out promptly and thoroughly with water
- wound which involve more than the superficial layers of skin should not be routinely treated
- repeated general skin cleansing of large body areas should not be done except when the underlying condition makes it necessary to reduce the bacterial population of the skin

Stop use and ask a doctor

if irritation, sensitization, or allergic reaction occurs. These may be signs of a serious conditions.

Keep out of reach of children

If swallowed, get medical help or contact a Poison Control Center right away.

Direction

- use with care in premature infants and infants under 2 months of age. These products may cause irritation or chemical burns.

Surgical hand scrub:

- wet hands and forearms under running water for 30 seconds. Clean fingernails using a nailstick or similar cleaner.
- scrub for 1.5 minutes with about 8 ml of product with or without a wet brush paying close attention to the nails, cuticles, and skin between the fingers
- rinse throughly under running water for 30 seconds
- wash for an additional 1.5 minutes with 8 ml of product and rinse under running water for 30 seconds
- dry thoroughly

Healthcare personnel handwash:

- wet hands with water
- dispense about 5 ml of product into cupped hands and wash in a vigorous manner for 15 minutes
- dry with sterile towel
- repeat procedure for an additional 2 minutes and dry with sterile towel

Patient preoperative skin preparation:

- apply product liberally to surgical site and swab for at least 2 minutes
- dry with sterile towel
- repeat procecedure for an additional 2 minutes and dry with sterile towel

Skin wound and general skin cleansing:

- thoroughly rinse the area to be cleaned with water
- apply the minimum amount of product necessary to cover the skin or wound area and wash gently
- rinse again thoroughly

other information

- store at 20-25 C (68-77 F)
- avoid excessive heat above 40 C (104 F)

Inactive ingredients

citric acid, cocamide DEA, hydroxyethylcellulose, isopropyl alcohol, lauramine oxide, purified water

Questions or comments?

Call 1-800-587-3271 Monday through Friday 8:00 AM to 4:30 PM

Package Label

NDC 0116-1021-04

DYNA-HEX 2®

(Chlorhexidine Gluconate 2% Solution)

Antispeptic

Contains: 2% Chlorhexidine Gluconate

Distributed By: Xttrium Laboratories, Inc., Mount Prospect, IL 60056

For External Use Only.

Net Contents: 4 fl OZ (118 mL)